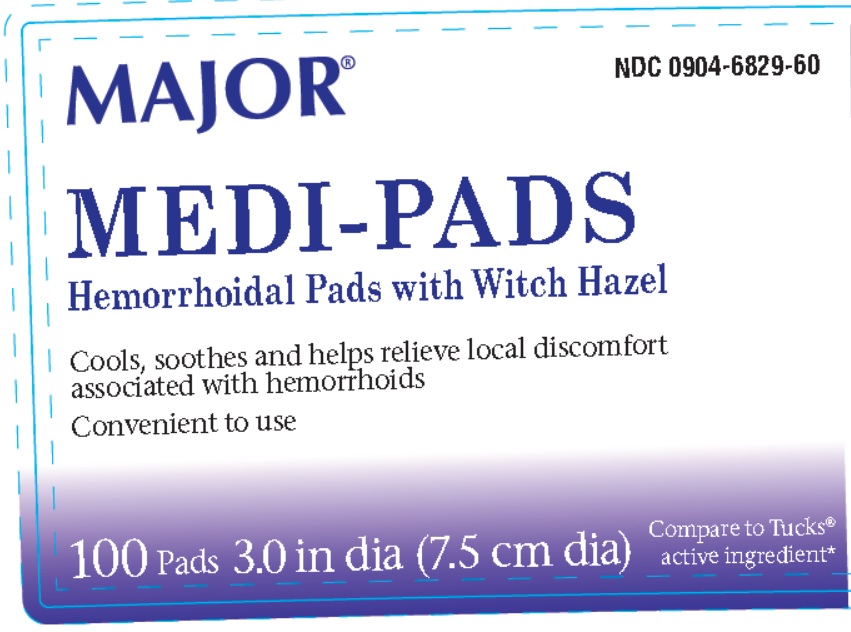 DRUG LABEL: Major Medi-Pads
NDC: 0904-6829 | Form: CLOTH
Manufacturer: Major Pharmaceuticals
Category: otc | Type: HUMAN OTC DRUG LABEL
Date: 20251205

ACTIVE INGREDIENTS: WITCH HAZEL 50 g/100 g
INACTIVE INGREDIENTS: ALCOHOL; GLYCERIN; PHENOXYETHANOL; ALOE; DECYL GLUCOSIDE; POTASSIUM SORBATE; PROPYLENE GLYCOL; SODIUM BENZOATE; CITRIC ACID MONOHYDRATE; WATER

MAJOR MEDI-PADS Hemorrhoidal Pads with Witch HAzel

Active Ingredient

Witch hazel 50%

Purpose

Astringent

Uses

- helps relieve the local itching and discomfort associated with hemorrhoids
- temporary relief of irritation and burning.
- aids in protecting irritated anorectal areas.

Warnings

For external use only.

When using this product

- do not exceed the recommended daily dosage unless directed by a doctor
- do not put this product into the rectum by using fingers or any mechanical device or applicator.

Stop use and ask a doctor if

- bleeding occurs
- condition worsens or does not improve within 7 days

Keep out of reach of children

If swallowed, get medical help or contact a Poison Control Center right away.(1-800-222-1222)

If pregnant or breast-feeding

ask a health professional before use.

Directions

- adult: Cleanse the area by gently wiping, patting or blotting. If necessary, repeat until all matter is removed from the area.
- apply externally to the affected area up to 6 times daily or after each bowel movement. After application, discard pad and wash hands.
- children under 12 years of age:Consult a doctor
- Dispose of pad in trash after use.
- Do not flush

Other information

- store at room temperature 15-30°C (59-86°F)

Inactive Ingredients

Water, Alcohol, Glycerin, Phenoxyethanol, Aloe, Decyl Glucoside, Potassium Sorbate, Propylene Glycol, Sodium Benzoate, Citric Acid

Questions or Comments?

(800) 616-2471

Principal Display Panel

NDC 0904-6829-60

MAJOR MEDI-PADS

Hemorrhoidal Pads with Witch Hazel

Cools, soothes and helps relieve local discomfort associated with hemorrhoids

Convenient to use

100 pads 3.0 in dia (7.5 cm dia)

Compare to Tucks active ingredient*

* This product is not manufactured or distrbiuted by McNEIL-PPC, Inc., owner of registered trademark Trucks